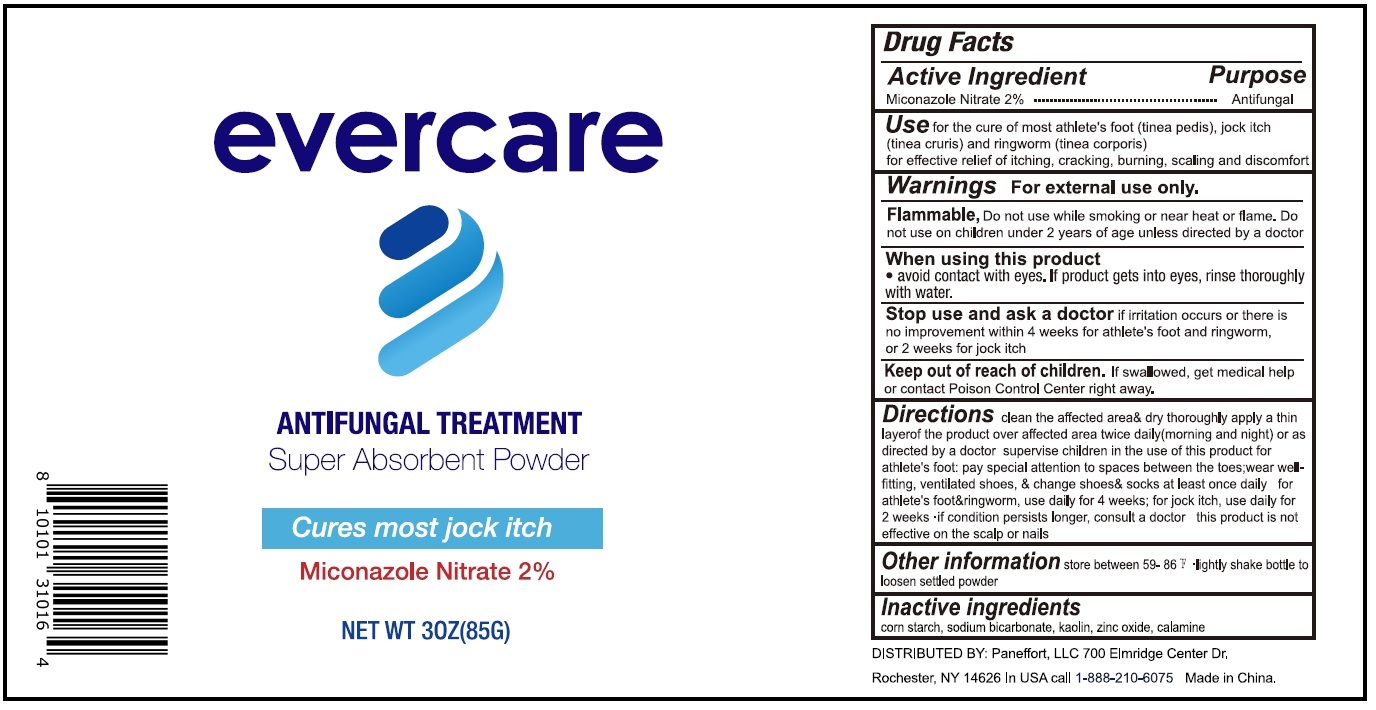 DRUG LABEL: Evercare Antifungal Treatment Super Absorbent Powder
NDC: 83099-000 | Form: POWDER
Manufacturer: PANEFFORT, LLC
Category: otc | Type: HUMAN OTC DRUG LABEL
Date: 20231026

ACTIVE INGREDIENTS: MICONAZOLE NITRATE 20 mg/1 g
INACTIVE INGREDIENTS: STARCH, CORN; SODIUM BICARBONATE; KAOLIN; ZINC OXIDE

Evercare Antifungal Treatment Super Absorbent Powder

Active Ingredient

Miconazole Nitrate 2%

Purpose

Antifungal

Use

for the cure of most athlete's foot (tinea pedis), jock itch (tinea cruris) and ringworm (tea corporis) for effective relief of itching, cracking, burning, scaling and discomfort

Warnings

For external use only.

Do not use while smoking or near heat or flame. Flammable,

Do not use

on children under 2 years of age unless directed by a doctor

When using this product

- avoid contact with eyes. If product gets into eyes, rinse thoroughly with water.

Stop use and ask a doctor

if irritation occurs or there is no improvement within 4 weeks for athlete's foot and ringworm, or 2 weeks for jock itch

Keep out of reach of children.

If swallowed, get medical help or contact Poison Control Center right away.

Directions

clean the affected area& dry thoroughly apply a thin layerof the product over affected area twice daily (morning and night) or as directed by a doctor supervise children in the use of this product for athlete's foot: pay special attenting to spaces between the toes;wear wellfitting, ventilated shoes, & change shoes& socks at least once daily for athlete's foot&ringworm, use daily for 4 weeks, for jock itch, use daily for 2 weeks if condition persists longer, consult a doctor this product is not effective on the scalp or nails

Other information

store between 59-86 °F

- lightly shake bottle to loosen settled powder

Inactive ingredients

corn starch, sodium bicarbonate, kaolin, zinc oxide, calamine